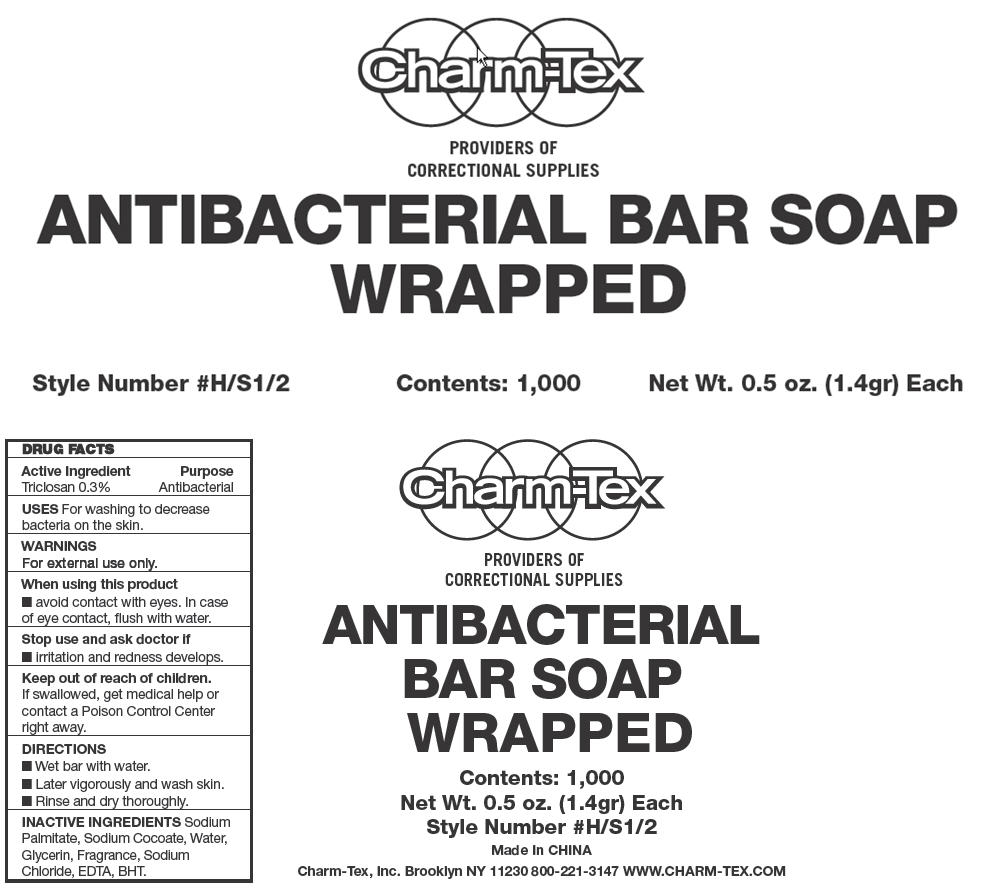 DRUG LABEL: Antibacterial Bar
NDC: 40057-3000 | Form: SOAP
Manufacturer: Charm-Tex, Inc
Category: otc | Type: HUMAN OTC DRUG LABEL
Date: 20121009

ACTIVE INGREDIENTS: Triclosan 0.3 g/100 g
INACTIVE INGREDIENTS: Sodium Palmitate; Sodium Cocoate; Water; Glycerin; Sodium Chloride; Edetic Acid

Antibacterial Bar Soap

DRUG FACTS

Active Ingredient

Triclosan 0.3%

Purpose

Antibacterial

USES

For washing to decrease bacteria on the skin.

WARNINGS

For external use only.

When using this product

- avoid contact with eyes. In case of eye contact, flush with water.

STOP USE

Stop use and ask doctor if

- irritation and redness develops.

Keep out of reach of children.

If swallowed, get medical help or contact a Poison Control Center right away.

DIRECTIONS

- Wet bar with water.
- Later vigorously and wash skin.
- Rinse and dry thoroughly.

INACTIVE INGREDIENTS

Sodium Palmitate, Sodium Cocoate, Water, Glycerin, Fragrance, Sodium Chloride, EDTA, BHT.

Charm-Tex, Inc. Brooklyn NY 11230

PRINCIPAL DISPLAY PANEL - 1.4 gr Bar Soap Carton

Charm-Tex

PROVIDERS OF
CORRECTIONAL SUPPLIES

ANTIBACTERIAL BAR SOAP
WRAPPED

Style Number #H/S1/2
Contents: 1,000
Net Wt. 0.5 oz. (1.4gr) Each